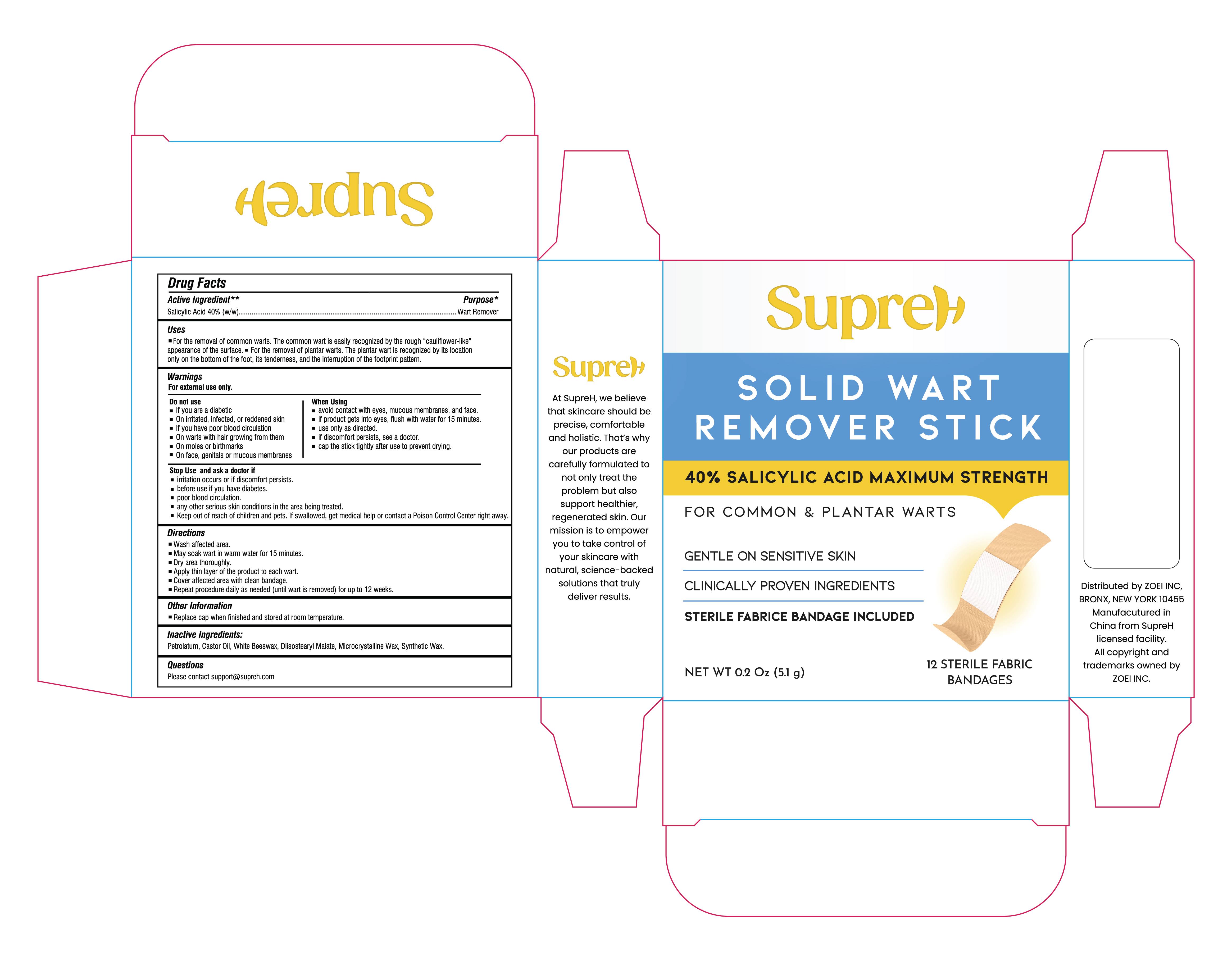 DRUG LABEL: SupreH Solid Wart Remover Stick
NDC: 83818-027 | Form: STICK
Manufacturer: Shenzhen Xinxin Yunhai Technology Co., Ltd.
Category: otc | Type: HUMAN OTC DRUG LABEL
Date: 20260129

ACTIVE INGREDIENTS: SALICYLIC ACID 40 g/100 1
INACTIVE INGREDIENTS: SYNTHETIC WAX (540 MW); CASTOR OIL; PETROLATUM; DIISOSTEARYL MALATE; MICROCRYSTALLINE WAX; WHITE WAX

83818-027

Active Ingredient

Salicylic Acid 40%

Purpose

Wart Remover

Use

For the removal of common warts. The common wart is easily recognized by the rough “cauliflower-like” appearance of the surface.
For the removal of plantar warts. The plantar wart is recognized by its location only on the bottom of the foot, its tenderness, and the interruption of the footprint pattern.

Warnings

For external use only

Do not use

If you are a diabetic
On irritated, infected, or reddened skin
If you have poor blood circulation
On warts with hair growing from them
On moles or birthmarks
On face, genitals or mucous membranes

When Using

avoid contact with eyes, mucous membranes, and face.
if product gets into eyes, flush with water for 15 minutes.
use only as directed.
if discomfort persists, see a doctor.
cap the stick tightly after use to prevent drying.

Stop Use and Ask a doctor if

irritation occurs or if discomfort persists

Ask Doctor

before use if you have
diabetes.
poor blood circulation.
any other serious skin conditions in the area being treated.

Keep out of reach of children and pets. If swallowed, get medical help or contact a Poison Control Center right away.

Directions

Wash affected area
May soak wart in warm water for 15 minutes
Dry area thoroughly
Apply thin layer of the product to each wart
Cover affected area with clean bandage
Repeat procedure daily as needed (until wart is removed) for up to 12 weeks

Other information

Replace cap when finished and stored at room temperature

Inactive ingredients

Petrolatum, Castor Oil, White Beeswax, Diisostearyl Malate, Microcrystalline Wax, Synthetic Wax

Questions

Please contact support@supreh.com